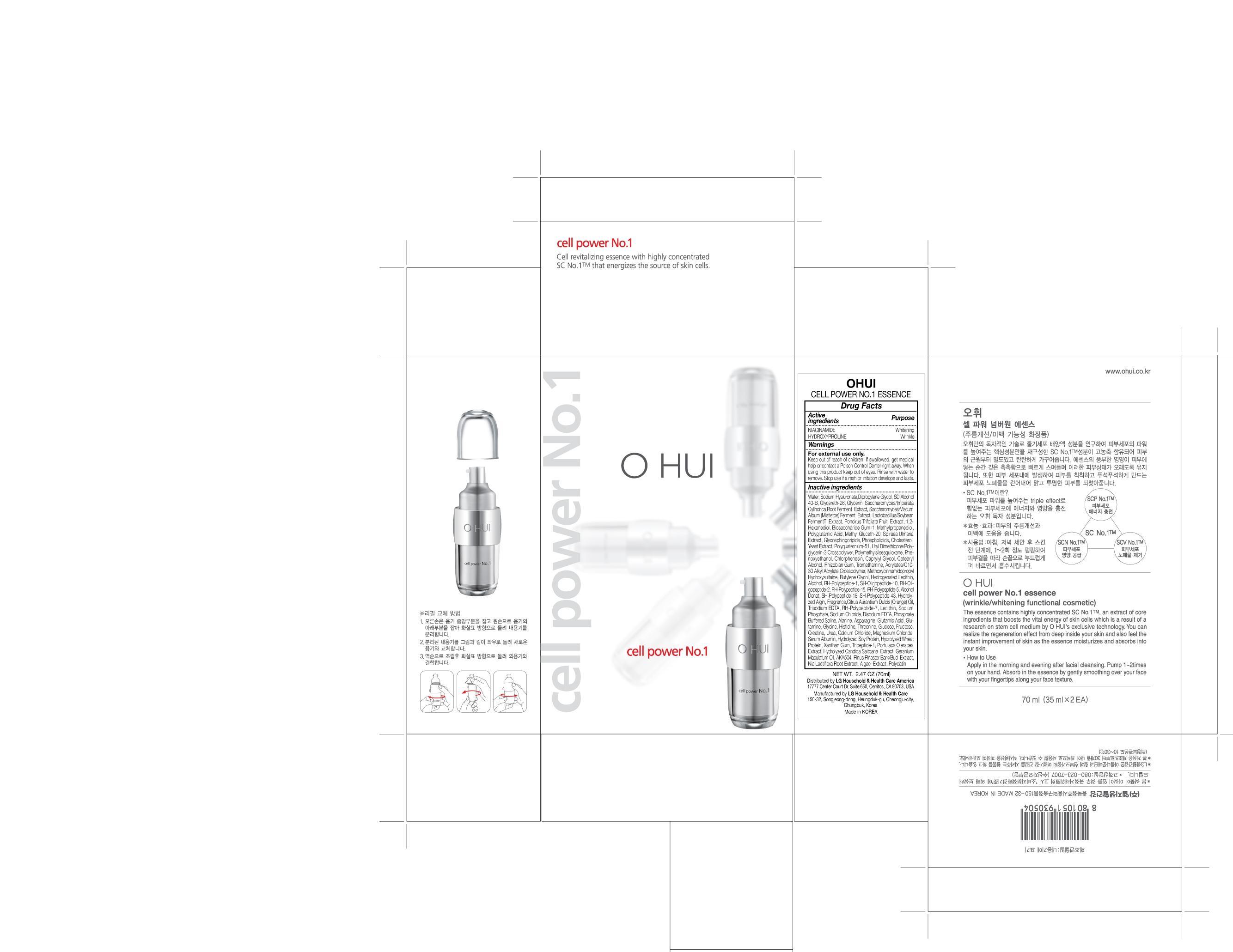 DRUG LABEL: OUHI CELL POWER NO 1 ESSENCE
NDC: 53208-491 | Form: LIQUID
Manufacturer: LG Household and Healthcare, Inc.
Category: otc | Type: HUMAN OTC DRUG LABEL
Date: 20101206

ACTIVE INGREDIENTS: NIACINAMIDE 2 mL/100 mL; HYDROXYPROLINE 0.5 mL/100 mL
INACTIVE INGREDIENTS: WATER; DIPROPYLENE GLYCOL; ALCOHOL; GLYCERETH-26; GLYCERIN; FRUIT; BIOSACCHARIDE GUM-1; METHYL GLUCETH-20; FILIPENDULA ULMARIA ROOT; YEAST; CETOSTEARYL ALCOHOL; TROMETHAMINE; EDETATE TRISODIUM; GERANIUM MACULATUM ROOT; PAEONIA LACTIFLORA ROOT; POLYDATIN

Drug Fact

ACTIVE INGREDIENT

NIACINAMIDE 2%
HYDROXYPROLINE 0.5%

PURPOSE

Wrinkle/Whitening functional cosmetic.

Stop use if rash or irritation develops and lasts.

WHEN USING

Keep out of eyes. Rinse with water to remove.

INDICATIONS AND USAGE

Apply in the morning and evening after facial cleansing. Pump 1~2 times on your hand. Absorb in the essence by gently smoothing over your face with your fingertips along your face texture.

Keep out of reach of children. Is swallowed, get medical help or contact a Poison Control Center right away.

INACTIVE INGREDIENT

WATER, DIPROPYLENE GLYCOL, ALCOHOL, GLYCERETH-26, GLYCERIN, FRUIT, BIOSACCHARIDE GUM-1, METHYL GLUCETH-20, FILIPENDULA ULMARIA ROOT, YEAST, CETOSTEARYL ALCOHOL, TROMETHAMINE, EDETATE TRISODIUM, GERANIUM MACULATUM ROOT, PAEONIA LACTIFLORA ROOT, POLYDATIN.

DOSAGE AND ADMINISTRATION

Use before the Skin or Toner.

PACKAGE LABEL

OHUI
CELL POWER NO.1
ESSENCE